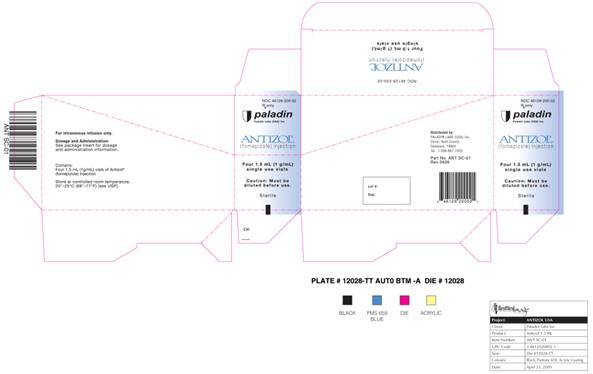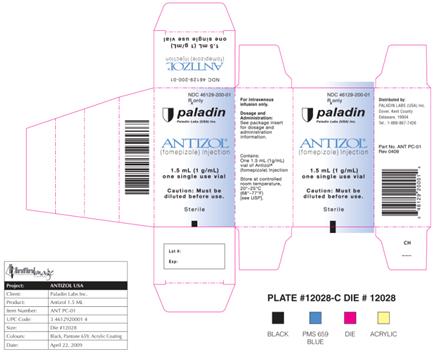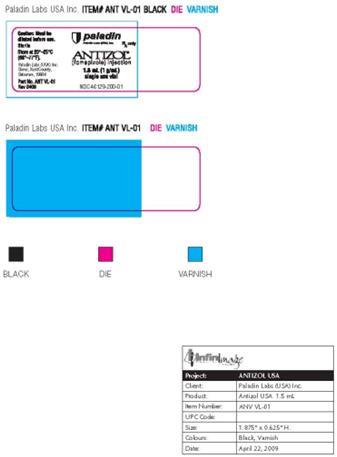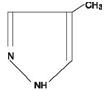 DRUG LABEL: Antizol
NDC: 46129-200 | Form: INJECTION
Manufacturer: PALADIN  LABORATORIES (USA) INC
Category: prescription | Type: Human Prescription Drug Label
Date: 20090727

ACTIVE INGREDIENTS: FOMEPIZOLE 1 g/1 mL

Sterile

Rx Only

Caution: Must be diluted prior to use.

DESCRIPTION

Antizol® (fomepizole) Injection is a competitive inhibitor of alcohol dehydrogenase.

The chemical name of fomepizole is 4-methylpyrazole. It has the molecular formula C4H6N2 and a molecular weight of 82.1. The structural formula is:

It is a clear to yellow liquid at room temperature. Its melting point is 25° C (77° F) and it may present as solid at room temperature. Fomepizole is soluble in water and very soluble in ethanol, diethyl ether, and chloroform. Each vial contains 1.5 mL (1 g/mL) of fomepizole.

CLINICAL PHARMACOLOGY

Mechanism of Action: Antizol® (fomepizole) is a competitive inhibitor of alcohol dehydrogenase. Alcohol dehydrogenase catalyzes the oxidation of ethanol to acetaldehyde. Alcohol dehydrogenase also catalyzes the initial steps in the metabolism of ethylene glycol and methanol to their toxic metabolites.

Ethylene glycol, the main component of most antifreezes and coolants, is metabolized to glycoaldehyde, which undergoes subsequent sequential oxidations to yield glycolate, glyoxylate, and oxalate. Glycolate and oxalate are the metabolic byproducts primarily responsible for the metabolic acidosis and renal damage seen in ethylene glycol toxicosis. The lethal dose of ethylene glycol in humans is approximately 1.4 mL/kg.

Methanol, the main component of windshield wiper fluid, is slowly metabolized via alcohol dehydrogenase to formaldehyde with subsequent oxidation via formaldehyde dehydrogenase to yield formic acid. Formic acid is primarily responsible for the metabolic acidosis and visual disturbances (e.g., decreased visual acuity and potential blindness) associated with methanol poisoning. A lethal dose of methanol in humans is approximately 1-2 mL/kg.

Fomepizole has been shown in vitro to block alcohol dehydrogenase enzyme activity in dog, monkey, and human liver. The concentration of fomepizole at which alcohol dehydrogenase is inhibited by 50% in vitro is approximately 0.1 μmol/L.

In a study of dogs given a lethal dose of ethylene glycol, three animals each were administered fomepizole, ethanol, or left untreated (control group). The three animals in the untreated group became progressively obtunded, moribund, and died. At necropsy, all three dogs had severe renal tubular damage. Fomepizole or ethanol, given 3 hours after ethylene glycol ingestion, attenuated the metabolic acidosis and prevented the renal tubular damage associated with ethylene glycol intoxication.

Several studies have demonstrated that Antizol® plasma concentrations of approximately 10μmol/L (0.82 mg/L) in monkeys are sufficient to inhibit methanol metabolism to formate, which is also mediated by alcohol dehydrogenase. Based on these results, concentrations of Antizol® in humans in the range of 100 to 300 μmol/L (8.6-24.6 mg/L) have been targeted to assure adequate plasma concentrations for the effective inhibition of alcohol dehydrogenase.

In healthy volunteers, oral doses of Antizol® (10-20 mg/kg) significantly reduced the rate of elimination of moderate doses of ethanol, which is also metabolized through the action of alcohol dehydrogenase (see PRECAUTIONS, Drug Interactions).

Pharmacokinetics: The plasma half-life of Antizol® varies with dose, even in patients with normal renal function, and has not been calculated.

Distribution: After intravenous infusion, Antizol® rapidly distributes to total body water. The volume of distribution is between 0.6 L/kg and 1.02 L/kg.

Metabolism: In healthy volunteers, only 1-3.5% of the administered dose of Antizol® (7-20 mg/kg oral and IV) was excreted unchanged in the urine, indicating that metabolism is the major route of elimination. In humans, the primary metabolite of Antizol® is 4-carboxypyrazole (approximately 80-85% of administered dose), which is excreted in the urine. Other metabolites of Antizol® observed in the urine are 4-hydroxymethylpyrazole and the N-glucuronide conjugates of 4-carboxypyrazole and 4-hydroxymethylpyrazole.

Excretion: The elimination of Antizol® is best characterized by Michaelis-Menten kinetics after acute doses, with saturable elimination occurring at therapeutic blood concentrations [100-300 μmol/L, 8.2-24.6 mg/L].

With multiple doses, Antizol® rapidly induces its own metabolism via the cytochrome P450 mixed-function oxidase system, which produces a significant increase in the elimination rate after about 30-40 hours. After enzyme induction, elimination follows first-order kinetics.

Special Populations:

Geriatric: Antizol® (fomepizole) Injection has not been studied sufficiently to determine whether the pharmacokinetics differ for a geriatric population.

Pediatric: Antizol® has not been studied sufficiently to determine whether the pharmacokinetics differ for a pediatric population.

Gender: Antizol® has not been studied sufficiently to determine whether the pharmacokinetics differ between the genders.

Renal Insufficiency: The metabolites of Antizol® are excreted renally. Definitive pharmacokinetic studies have not been done to assess pharmacokinetics in patients with renal impairment.

Hepatic Insufficiency: Antizol® is metabolized through the liver, but no definitive pharmacokinetic studies have been done in subjects with hepatic disease.

Clinical Studies: The efficacy of Antizol® in the treatment of ethylene glycol and methanol intoxication was studied in two prospective, U.S. clinical trials without concomitant control groups. Fourteen of 16 patients in the ethylene glycol trial and 7 of 11 patients in the methanol trial underwent hemodialysis because of severe intoxication (see DOSAGE AND ADMINISTRATION). All patients received Antizol® shortly after admission.

The results of these two studies provide evidence that Antizol® blocks ethylene glycol and methanol metabolism mediated by alcohol dehydrogenase in the clinical setting. In both studies, plasma concentrations of toxic metabolites of ethylene glycol and methanol failed to rise in the initial phases of treatment. The relationship to Antizol® therapy, however, was confounded by hemodialysis and significant blood ethanol concentrations in many of the patients. Nevertheless, in the post-dialysis period(s), when ethanol concentrations were insignificant and the concentrations of ethylene glycol or methanol were > 20 mg/dL, the administration of Antizol® alone blocked any rise in glycolate or formate concentrations, respectively.

In a separate French trial, 5 patients presented with ethylene glycol concentrations ranging from 46.5 to 345 mg/dL, insignificant ethanol blood concentrations, and normal renal function. These patients were treated with fomepizole alone without hemodialysis, and none developed signs of renal injury.

INDICATIONS AND USAGE

Antizol® is indicated as an antidote for ethylene glycol (such as antifreeze) or methanol poisoning, or for use in suspected ethylene glycol or methanol ingestion, either alone or in combination with hemodialysis (see DOSAGE AND ADMINISTRATION).

CONTRAINDICATIONS

Antizol® should not be administered to patients with a documented serious hypersensitivity reaction to Antizol® or other pyrazoles.

PRECAUTIONS

General

Antizol® should not be given undiluted or by bolus injection. Venous irritation and phlebosclerosis were noted in two of six normal volunteers given bolus injections (over 5 minutes) of Antizol® at a concentration of 25 mg/mL.

Minor allergic reactions (mild rash, eosinophilia) have been reported in a few patients receiving Antizol® (see ADVERSE REACTIONS). Therefore, patients should be monitored for signs of allergic reactions.

Laboratory Tests

In addition to specific antidote treatment with Antizol®, patients intoxicated with ethylene glycol or methanol must be managed for metabolic acidosis, acute renal failure (ethylene glycol), adult respiratory distress syndrome, visual disturbances (methanol), and hypocalcemia. Fluid therapy and sodium bicarbonate administration are potential supportive therapies. In addition, potassium and calcium supplementation and oxygen administration are usually necessary. Hemodialysis is necessary in the anuric patient, or in patients with severe metabolic acidosis or azotemia (see DOSAGE AND ADMINISTRATION). Treatment success should be assessed by frequent measurements of blood gases, pH, electrolytes, BUN, creatinine, and urinalysis, in addition to other laboratory tests as indicated by individual patient conditions. At frequent intervals throughout the treatment, patients poisoned with ethylene glycol should be monitored for ethylene glycol concentrations in serum and urine, and the presence of urinary oxalate crystals. Similarly, serum methanol concentrations should be monitored in patients poisoned with methanol. Electrocardiography should be performed because acidosis and electrolyte imbalances can affect the cardiovascular system. In the comatose patient, electroencephalography may also be required. In addition, hepatic enzymes and white blood cell counts should be monitored during treatment, as transient increases in serum transaminase concentrations and eosinophilia have been noted with repeated Antizol® dosing.

Drug Interactions

Oral doses of Antizol® (10-20 mg/kg), via alcohol dehydrogenase inhibition, significantly reduced the rate of elimination of ethanol (by approximately 40%) given to healthy volunteers in moderate doses. Similarly, ethanol decreased the rate of elimination of Antizol® (by approximately 50%) by the same mechanism.

Reciprocal interactions may occur with concomitant use of Antizol® and drugs that increase or inhibit the cytochrome P450 system (e.g., phenytoin, carbamazepine, cimetidine, ketoconazole), though this has not been studied.

Carcinogenesis, Mutagenesis, and Impairment of Fertility

There have been no long-term studies performed in animals to evaluate carcinogenic potential. There was a positive Ames test result in the Escherichia coli tester strain WP2uvrA and the Salmonella typhimurium tester strain TA102 in the absence of metabolic activation.

There was no evidence of a clastogenic effect in the in vivo mouse micronucleus assay.

In rats, fomepizole (110 mg/kg) administered orally for 40 to 42 days resulted in decreased testicular mass (approximately 8% reduction). This dose is approximately 0.6 times the human maximum daily exposure based on surface area (mg/m2). This reduction was similar for rats treated with either ethanol or fomepizole alone. When fomepizole was given in combination with ethanol, the decrease in testicular mass was significantly greater (approximately 30% reduction) compared to those rats treated exclusively with fomepizole or ethanol.

Pregnancy

Pregnancy Category C: Animal reproduction studies have not been conducted with fomepizole. It is also not known whether Antizol® can cause fetal harm when administered to pregnant women or can affect reproduction capacity. Antizol® should be given to pregnant women only if clearly needed.

Nursing Mothers

It is not known whether fomepizole is excreted in human milk. Because many drugs are excreted in human milk, caution should be exercised when Antizol® is administered to a nursing woman.

Pediatric Use

Safety and effectiveness in pediatric patients have not been established.

Geriatric Use

Safety and effectiveness in geriatric patients have not been established.

ADVERSE REACTIONS

The most frequent adverse events reported as drug-related or unknown relationship to study drug in the 78 patients and 63 normal volunteers who received Antizol® (fomepizole) Injection were headache (14%), nausea (11%), and dizziness, increased drowsiness, and bad taste/metallic taste (6% each). All other adverse events in this population were reported in approximately 3% or fewer of those receiving Antizol® and were as follows:

Body as a Whole: Abdominal pain, fever, multiorgan system failure, pain during Antizol® injection, inflammation at injection site, lumbalgia/backache, hangover

Cardiovascular: Sinus bradycardia/bradycardia, phlebosclerosis, tachycardia, phlebitis, shock, hypotension

Gastrointestinal: Vomiting, diarrhea, dyspepsia, heartburn, decreased appetite, transient transaminitis

Hemic/Lymphatic: Eosinophilia/hypereosinophilia, lymphangitis, disseminated intravascular coagulation, anemia

Nervous: Lightheadedness, seizure, agitation, feeling drunk, facial flush, vertigo, nystagmus, anxiety, “felt strange”, decreased environmental awareness

Respiratory: Hiccups, pharyngitis

Skin/Appendages: Application site reaction, rash

Special Senses: Abnormal smell, speech/visual disturbances, transient blurred vision, roar in ear

Urogenital: Anuria

OVERDOSAGE

Nausea, dizziness, and vertigo were noted in healthy volunteers receiving 50 and 100 mg/kg doses of Antizol® (at plasma concentrations of 290-520 μmol/L, 23.8-42.6 mg/L). These doses are 3-6 times the recommended dose. This dose-dependent CNS effect was short-lived in most subjects and lasted up to 30 hours in one subject.

Antizol® is dialyzable, and hemodialysis may be useful in treating cases of overdosage.

DOSAGE AND ADMINISTRATION

Treatment Guidelines: If ethylene glycol or methanol poisoning is left untreated, the natural progression of the poisoning leads to accumulation of toxic metabolites, including glycolic and oxalic acids (ethylene glycol intoxication) and formic acid (methanol intoxication). These metabolites can induce metabolic acidosis, nausea/ vomiting, seizures, stupor, coma, calcium oxaluria, acute tubular necrosis, blindness, and death. The diagnosis of these poisonings may be difficult because ethylene glycol and methanol concentrations diminish in the blood as they are metabolized to their respective metabolites. Hence, both ethylene glycol and methanol concentrations and acid base balance, as determined by serum electrolyte (anion gap) and/or arterial blood gas analysis, should be frequently monitored and used to guide treatment.

Treatment consists of blocking the formation of toxic metabolites using inhibitors of alcohol dehydrogenase, such as Antizol®, and correction of metabolic abnormalities. In patients with high ethylene glycol or methanol concentrations (≥ 50 mg/dL), significant metabolic acidosis, or renal failure, hemodialysis should be considered to remove ethylene glycol or methanol and the respective toxic metabolites of these alcohols.

Treatment with Antizol®:

Begin Antizol® treatment immediately upon suspicion of ethylene glycol or methanol ingestion based on patient history and/or anion gap metabolic acidosis, increased osmolar gap, visual disturbances, or oxalate crystals in the urine, OR a documented serum ethylene glycol or methanol concentration greater than 20 mg/dL.

Hemodialysis: Hemodialysis should be considered in addition to Antizol® in the case of renal failure, significant or worsening metabolic acidosis, or a measured ethylene glycol or methanol concentration of greater than or equal to 50 mg/dL. Patients should be dialyzed to correct metabolic abnormalities and to lower the ethylene glycol concentrations below 50 mg/dL.

Discontinuation of Antizol® Treatment: Treatment with Antizol® may be discontinued when ethylene glycol or methanol concentrations are undetectable or have been reduced below 20 mg/dL, and the patient is asymptomatic with normal pH.

Dosing of Antizol®: A loading dose of 15 mg/kg should be administered, followed by doses of 10 mg/kg every 12 hours for 4 doses, then 15 mg/kg every 12 hours thereafter until ethylene glycol or methanol concentrations are undetectable or have been reduced below 20 mg/dL, and the patient is asymptomatic with normal pH. All doses should be administered as a slow intravenous infusion over 30 minutes (see Administration).

Dosage with Renal Dialysis: Antizol® (fomepizole) Injection is dialyzable and the frequency of dosing should be increased to every 4 hours during hemodialysis

Antizol® Dosing in Patients Requiring Hemodialysis
DOSE AT THE BEGINNING OF HEMODIALYSIS
If <6 hours since last Antizol® dose | If ≥ 6 hours since last Antizol® dose
Do not administer dose | Administer next scheduled dose

DOSING DURING HEMODIALYSIS

Dose every 4 hours

DOSING AT THE TIME HEMODIALYSIS IS COMPLETED
Time between last dose and the end of hemodialysis
<1 hour | Do not administer dose at the end of hemodialysis
1-3 hours | Administer 1/2 of next scheduled dose
>3 hours | Administer next scheduled dose

MAINTENANCE DOSING OFF HEMODIALYSIS

Give next scheduled dose 12 hours from last dose administered

Administration: Antizol® solidifies at temperatures less than 25° C (77° F). If the Antizol® solution has become solid in the vial, the solution should be liquefied by running the vial under warm water or by holding in the hand. Solidification does not affect the efficacy, safety, or stability of Antizol®. Using sterile technique, the appropriate dose of Antizol® should be drawn from the vial with a syringe and injected into at least 100 mL of sterile 0.9% sodium chloride injection or dextrose 5% injection. Mix well. The entire contents of the resulting solution should be infused over 30 minutes. Antizol®, like all parenteral products, should be inspected visually for particulate matter prior to administration.

Stability: Antizol® diluted in 0.9% sodium chloride injection or dextrose 5% injection remains stable and sterile for at least 24 hours when stored refrigerated or at room temperature. Antizol® does not contain preservatives. Therefore, maintain sterile conditions, and after dilution do not use beyond 24 hours. Solutions showing haziness, particulate matter, precipitate, discoloration, or leakage should not be used.

HOW SUPPLIED

Antizol® is supplied as a sterile, preservative-free solution for intravenous use as:

Supplied in packages of four vials or one vial. Each vial contains 1.5 mL (1 g/mL) of fomepizole.

NDC 46129-200-02 (four vials)

NDC 46129-200-01 (one vial)

Store at controlled room temperature, 20° to 25° C (68° to 77° F)

Distributed in the U.S. by:
Paladin Labs (USA) Inc.

Dover, Kent County,
Delaware, 19904
For questions of a medical nature, call 1-888-867-7426.
Part No. ANT PI-8511
Revision Date: April 2009

PACKAGE LABEL.PRINCIPAL DISPLAY PANEL- 1.5 mL (4 vials)

NDC 46129-200-02
Rx only
ANTIZOL® (fomepizole) Injection
Four 1.5 mL (1 g/mL)
single use vials
Caution: Must be diluted before use

PACKAGE LABEL.PRINCIPAL DISPLAY PANEL- 1.5 mL (1 Vial)

NDC 46129-200-01
Rx only
ANTIZOL® (fomepizole) Injection
1.5 mL (1 g/mL)
one single use vial
Caution: Must be diluted before use

PACKAGE LABEL.PRINCIPAL DISPLAY PANEL- 1.5 mL (1 vial)

NDC 46129-200-01
Rx only
ANTIZOL® (fomepizole) Injection
1.5 mL (1 g/mL)
single use vial